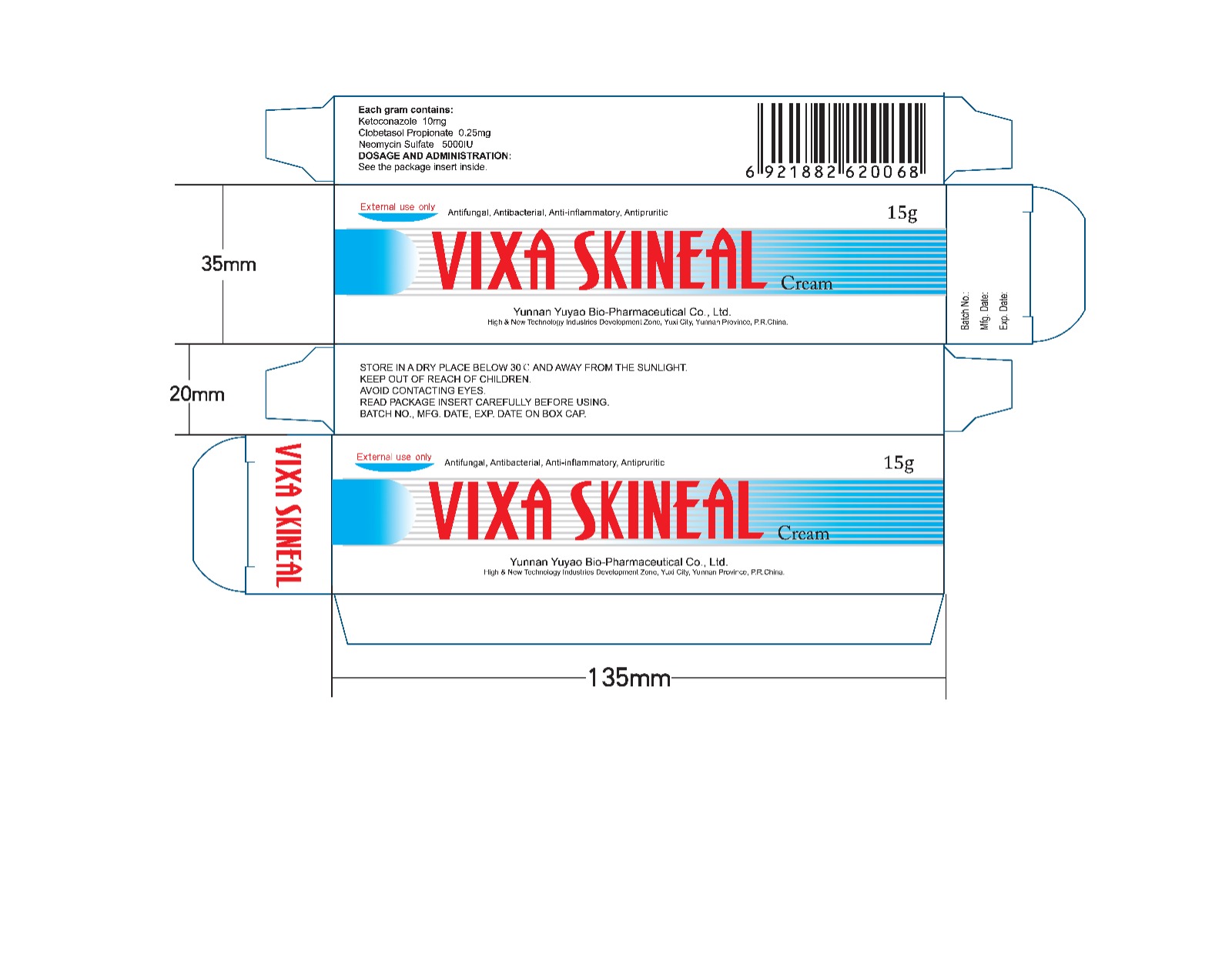 DRUG LABEL: Vixa Skineal
NDC: 84659-9040 | Form: CREAM
Manufacturer: Yunnan Yuyao Bio-pharmaceutical Co.,Ltd.
Category: prescription | Type: HUMAN PRESCRIPTION DRUG LABEL
Date: 20250205

ACTIVE INGREDIENTS: CLOBETASOL PROPIONATE 0.25 mg/1 g; NEOMYCIN SULFATE 5000 [iU]/1 g; KETOCONAZOLE 10 mg/1 g

DOSAGE AND ADMINISTRATION:
Apply externally to affected area twice daily. It is suggested to use for 2 weeks on ordinary tinea corporis and tinea cruris, for 4 weeks on tinea pedis and tinea manus.
SIDE EFFECTS:
VIXA SKINEAL has few side effects when used topically. A few instance of irritation or burning sensation may be observed occasionally during the treatment. But usually, it is unnecessary to stop the drug.
CONTRAINDICATION:

PACKAGE LABEL

DESCRIPTION:
A white or off-white cream with emulsive base.
PHARMACOLOGICAL ACTIONS:
Ketoconazole is a broad-spectrum anti-fungal agent that acts on the cell membranes of fungi by changing its permeability. Pharmacological studies have shown that Ketoconazole has extremely potent antimycotic actions against dermatophytes (such as Trichophyton sp., Microsporum sp., and epidermophyton sp.), saccharomyces and candida albicans. Strains of fungi are unlikely to have a natural resistance to Ketoconazole. Clobetasol Propionate is cortex hormone that is highly effective as an anti-inflammatory and anti-allergic agent with a few side effects. Neomycin Sulfate is effective against Gram-positive cocci and Gram-negative bacilli. As a result, this compound cream is jointly effective against fungus, bacteria, inflammation and pruritus.
INDICATIONS:
VIXA SKINEAL is indicated for topical application on the treatment of fungal infection of skin, such as tinea manus, tinea pedis, tinea corporis, tinea cruris and tinea versicolor. It is also proved effective on the treatment of many kinds of dermatitis, eczema and pruritus.
DOSAGE AND ADMINISTRATION:
Apply externally to affected area twice daily. It is suggested to use for 2 weeks on ordinary tinea corporis and tinea cruris, for 4 weeks on tinea pedis and tinea manus.
SIDE EFFECTS:
VIXA SKINEAL has few side effects when used topically. A few instance of irritation or burning sensation may be observed occasionally during the treatment. But usually, it is unnecessary to stop the drug.
CONTRAINDICATION:
VIXA SKINEAL is contraindicated in patients with known hypersensitivity to any of its ingredients. It is not for ophthalmic use. Take special precautions when using on pregnancy and infancy.
PRECAUTIONS:
It should be under doctor's supervision to apply VIXA SKINEAL on the face or on large areas for a long period of time.
PACKAGE:
Each tube contains 15g.
STORAGE:
STORE IN A DRY PLACE BELOW 30°C AND AWAY FROM THE SUNLIGHT.
EXPIRATION DATE:
Three years after the manufacturing date.
FOR EXTERNAL USE ONLY. KEEP OUT OF REACH OF CHILDREN. AVOID CONTACTING EYES.
READ PACKAGE INSERT CAREFULLY BEFORE USING. BATCH NO., MFG. DATE, EXP. DATE ON BOX CAP.
Mfg. by: Yunnan Yuyao Bio-Pharmaceutical Co., Ltd.
Address: High & New Technology Industries Development Zone, Yuxi City, Yunnan Province, P.R.China.